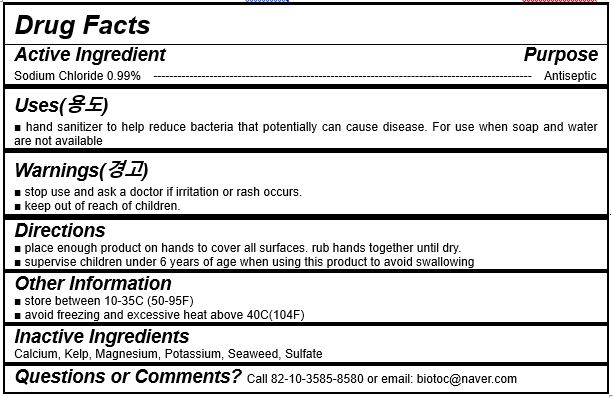 DRUG LABEL: Detox  toc toc
NDC: 87414-0001 | Form: POWDER
Manufacturer: Korea Life Science
Category: otc | Type: HUMAN OTC DRUG LABEL
Date: 20260108

ACTIVE INGREDIENTS: MAGNESIUM 4.95 g/500 g
INACTIVE INGREDIENTS: NORI; CALCIUM; POTASSIUM; SULFATE ION; WATER

ACTIVE INGREDIENT

Sodium Chloride

INACTIVE INGREDIENT

Kelp extract, Seaweed extract, magnesium extract, calcium extract, potassium extract, sulfate ion extract, water

PURPOSE

Hand sanitizer to help reduce bacteria that potentially can cause disease. for use when soap and water are not available.

keep out of reach of the children

INDICATIONS AND USAGE

place enough product on hadns to cover all surfaces. rub hands together until dry.

supervise children uner 6 years of age when using this product to avoid swallowing.

Stop use and ask a doctor if irritation or rash occurs.

Keep out of reach of children.

DOSAGE AND ADMINISTRATION

for external use only